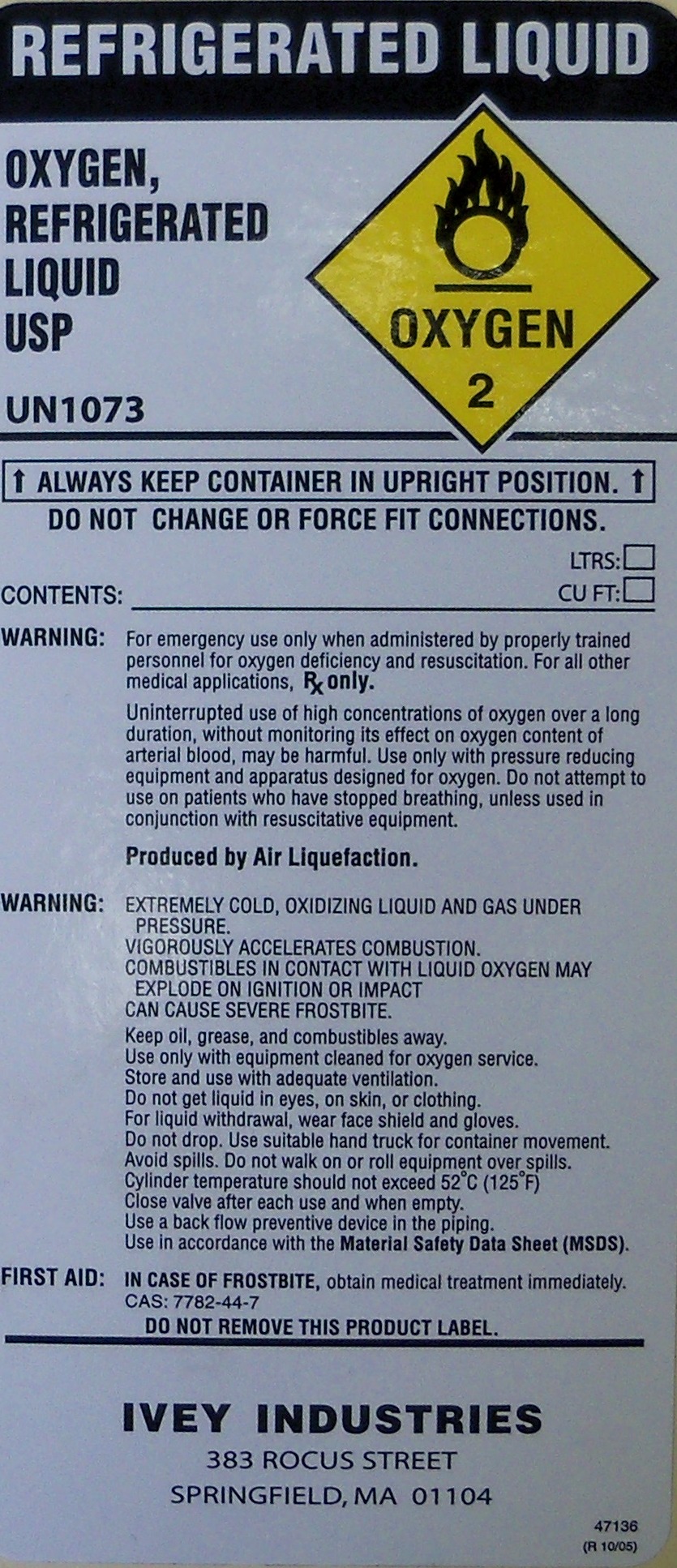 DRUG LABEL: oxygen
NDC: 55065-002 | Form: GAS
Manufacturer: Ivey Industries
Category: prescription | Type: HUMAN PRESCRIPTION DRUG LABEL
Date: 20100503

ACTIVE INGREDIENTS: oxygen 992 L/1000 L

OXYGEN REFRIGERATED LIQUID USP

PACKAGE LABEL

OXYGEN REFRIGERATED LIQUID USP
UN 1073